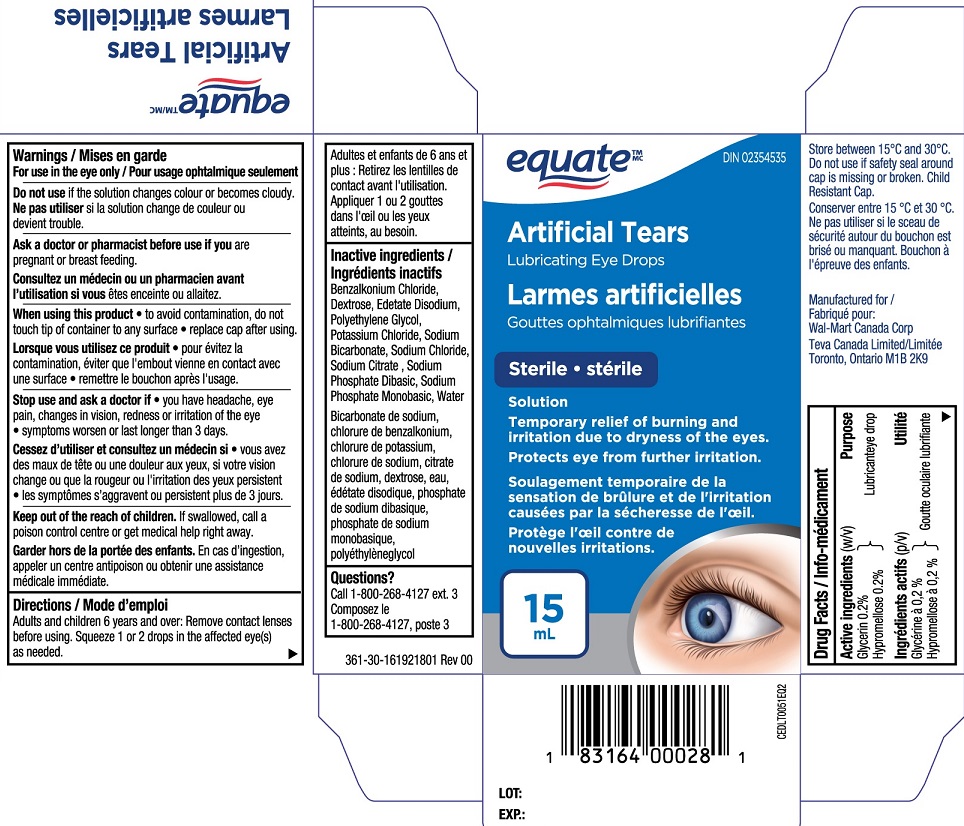 DRUG LABEL: Equate Artificial Tears
NDC: 55651-033 | Form: SOLUTION
Manufacturer: KC Pharmaceuticals, Inc.
Category: otc | Type: HUMAN OTC DRUG LABEL
Date: 20251231

ACTIVE INGREDIENTS: GLYCERIN 0.2 g/100 mL; HYPROMELLOSE, UNSPECIFIED 0.2 g/100 mL
INACTIVE INGREDIENTS: BENZALKONIUM CHLORIDE; WATER; EDETATE DISODIUM; SODIUM CHLORIDE; SODIUM CITRATE; DEXTROSE; POLYETHYLENE GLYCOL, UNSPECIFIED; SODIUM PHOSPHATE, MONOBASIC; POTASSIUM CHLORIDE; SODIUM BICARBONATE; SODIUM PHOSPHATE, DIBASIC

Equate Artificial Tears 15 mL (MFR - EXPORT)